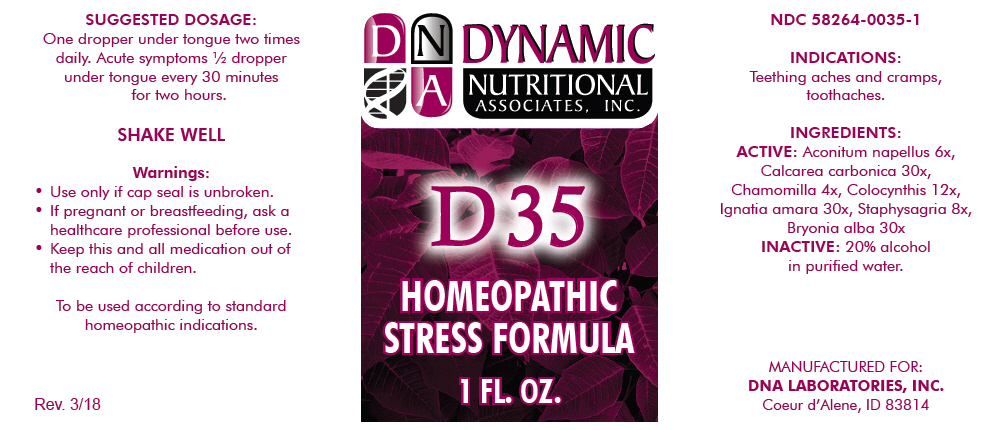 DRUG LABEL: D-35
NDC: 58264-0035 | Form: SOLUTION
Manufacturer: DNA Labs, Inc.
Category: homeopathic | Type: HUMAN OTC DRUG LABEL
Date: 20250113

ACTIVE INGREDIENTS: ACONITUM NAPELLUS 6 [hp_X]/1 mL; OYSTER SHELL CALCIUM CARBONATE, CRUDE 30 [hp_X]/1 mL; MATRICARIA CHAMOMILLA 4 [hp_X]/1 mL; CITRULLUS COLOCYNTHIS FRUIT PULP 12 [hp_X]/1 mL; STRYCHNOS IGNATII SEED 30 [hp_X]/1 mL; DELPHINIUM STAPHISAGRIA SEED 8 [hp_X]/1 mL; BRYONIA ALBA ROOT 30 [hp_X]/1 mL
INACTIVE INGREDIENTS: ALCOHOL; WATER

D-35

NDC 58264-0035-1

INDICATIONS

PURPOSE

Teething aches and cramps, toothaches.

INGREDIENTS

ACTIVE

Aconitum napellus 6x, Calcarea carbonica 30x, Chamomilla 4x, Colocynthis 12x, Ignatia amara 30x, Staphysagria 8x, Bryonia alba 30x

INACTIVE

20% alcohol in purified water.

SUGGESTED DOSAGE

One dropper under tongue two times daily. Acute symptoms ½ dropper under tongue every 30 minutes for two hours.

STORAGE AND HANDLING

SHAKE WELL

Warnings

- Use only if cap seal is unbroken.

PREGNANCY OR BREAST FEEDING

- If pregnant or breastfeeding, ask a healthcare professional before use.

KEEP OUT OF REACH OF CHILDREN

- Keep this and all medication out of the reach of children.

To be used according to standard homeopathic indications.

PRINCIPAL DISPLAY PANEL - 1 FL. OZ. Bottle Label

DYNAMIC
NUTRITIONAL
ASSOCIATES, INC.

D 35

HOMEOPATHIC
STRESS FORMULA

1 FL. OZ.